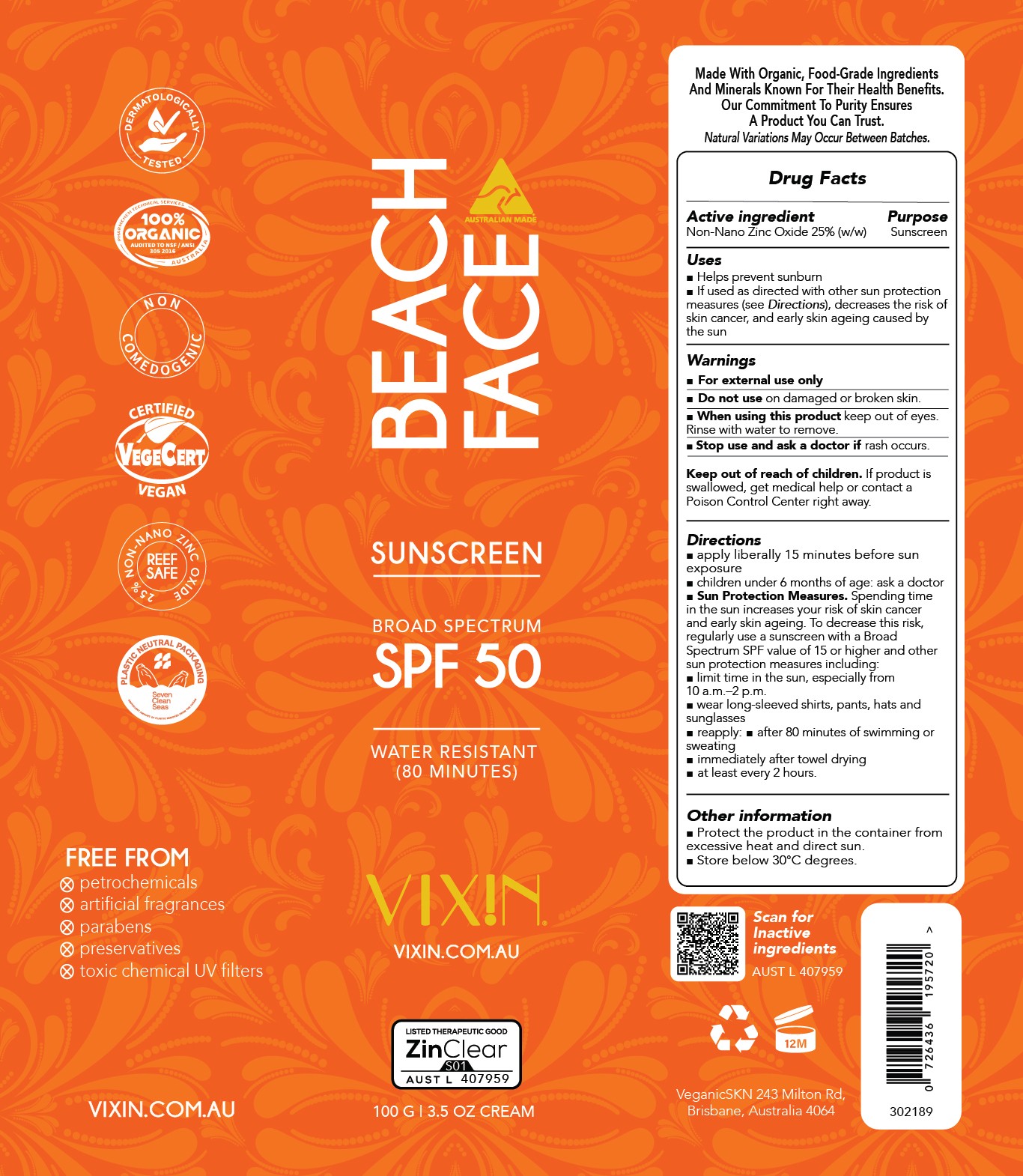 DRUG LABEL: Vixin Beach Face Sunscreen SPF50
NDC: 83252-146 | Form: CREAM
Manufacturer: Veganic SKN Limited
Category: otc | Type: HUMAN OTC DRUG LABEL
Date: 20260112

ACTIVE INGREDIENTS: ZINC OXIDE 25 kg/100 kg
INACTIVE INGREDIENTS: CITRUS PARADISI SEED; WATER; POLYHYDROXYSTEARIC ACID (2300 MW); SODIUM CHLORIDE; JOJOBA OIL; HIPPOPHAE RHAMNOIDES SEED OIL; HYALURONATE SODIUM; SODIUM HINOKITIOL; CALENDULA OFFICINALIS FLOWER; FERRIC OXIDE RED; CANDELILLA WAX; ISOSTEARIC ACID; GLYCERIN; KAKADU PLUM; TOCOPHEROL; SUNFLOWER OIL; MALTODEXTRIN; .ALPHA.-BISABOLOL, (+/-)-; FERRIC OXIDE YELLOW; POLYGLYCERYL-3 RICINOLEATE; POTASSIUM CETYL PHOSPHATE; XANTHAN GUM; SODIUM ASCORBATE; CORIANDER OIL; FERROSOFERRIC OXIDE

Vixin Beach Face Sunscreen SPF50

ACTIVE INGREDIENT

Zinc oxide 25%

PURPOSE

Sunscreen

INDICATIONS AND USAGE

Please kindly refer to artwork

WARNINGS

For external use only.
Do not use on damaged r broken skin.
When using this product keep out of eyes. Rinse with water to remove. Stop use and ask a
doctor if rash occurs.
Keep out of reach of children.
If product is swallowed, get medical help or contact a Poison Control Center right away.

Keep out of reach of children

DOSAGE AND ADMINISTRATION

Please kindly refer to artwork

INACTIVE INGREDIENT

Please kindly refer to artwork